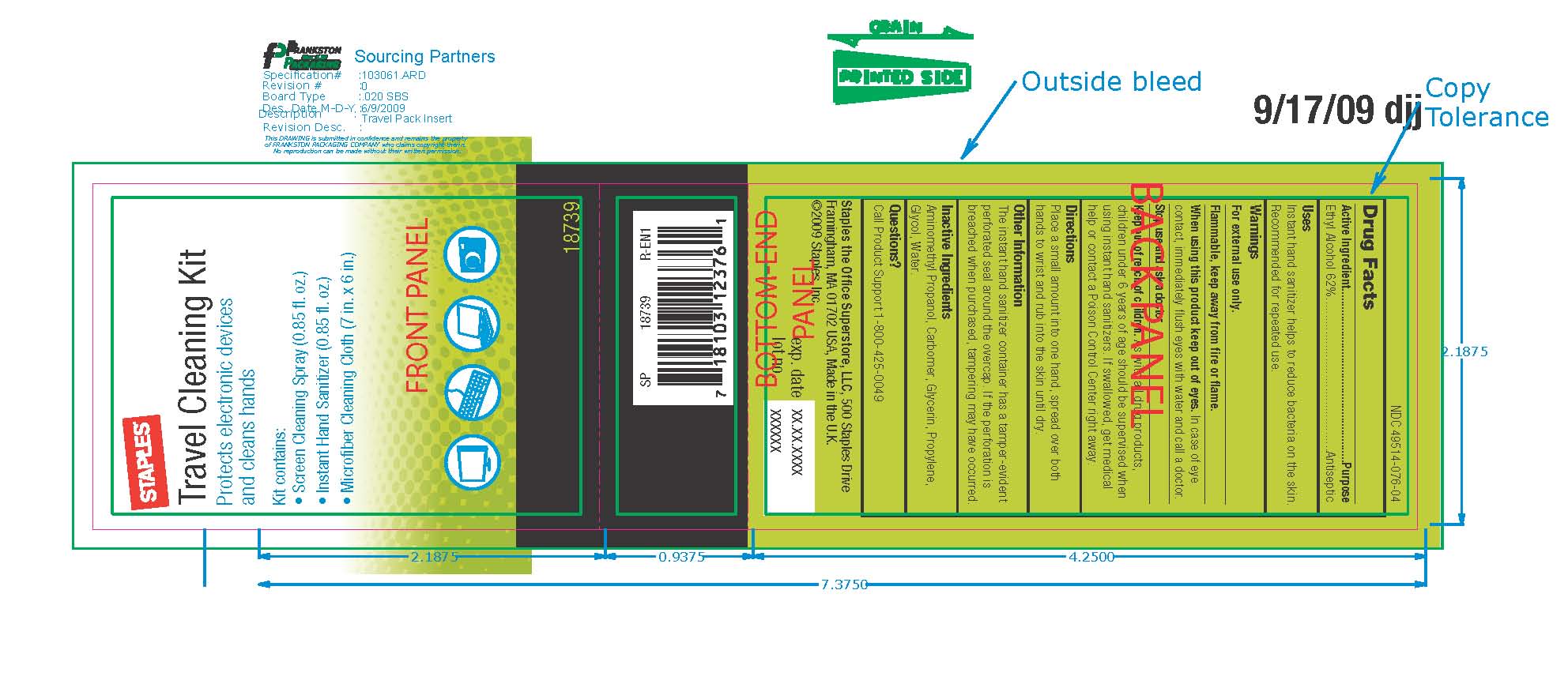 DRUG LABEL: Staples Instant Hand Sanitizer
NDC: 49514-076 | Form: GEL
Manufacturer: Staples
Category: otc | Type: HUMAN OTC DRUG LABEL
Date: 20090928

ACTIVE INGREDIENTS: Alcohol 62 mL/100 mL
INACTIVE INGREDIENTS: 2-AMINO-2-METHYL-1-PROPANOL; CARBOMER HOMOPOLYMER TYPE C; Glycerin; Propylene Glycol; Water

Staples Travel Cleaning Kit

Drug Facts

Active Ingredient Purpose

Ethyl Alcohol 62 percent Antiseptic

Uses

Instant hand sanitizer helps to reduce bacteria on the skin.

Recommended for repeated use.

Warnings

For external use only.

SAFE HANDLING WARNING

Flammable , keep away from fire or flame.

When using this product keep out of eyes.

In case of eye contact, immediately flush eyes with water and call a doctor.

Stop use and ask a doctor.

Keep out of reach of children.

As with all drug products,

children under 6 years of ages should be supervised when

using instant hand sanitizers. If swallowed, get medical

help or contact a Poison Control Center right away.

Directions

Place a small amount into one hand, spread over both

hands to wrist and rub into the skin until dry.

Other Information

The instant hand sanitizer container has a tamper-evident

perforated seal around the overcap. If the perforation is

breached when purchased, tampering may have occurred.

Inactive Ingredients

Aminomethyl Propanol , Carbomer , Glycerin , Propylene ,

Glycol , Water.

Questions

Call Product Support 1 800 425 0049

DESCRIPTION

Staples the Office Superstore, LLC

500 Staples Drive

Framingham, MA 01702 USA

Made in UK

2009 Staples, Inc.

exp date

lot no

PACKAGE LABEL

Staples

Travel Cleaning Kit

Protects electronic devices and cleans hands

Kit contains:

1 small Microfiber Cleaning Cloth

1 Instant Hand Sanitizer 0.85 fl oz

1 Screen Cleaning Spray 0.85 fl oz